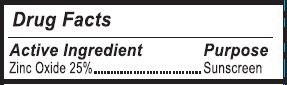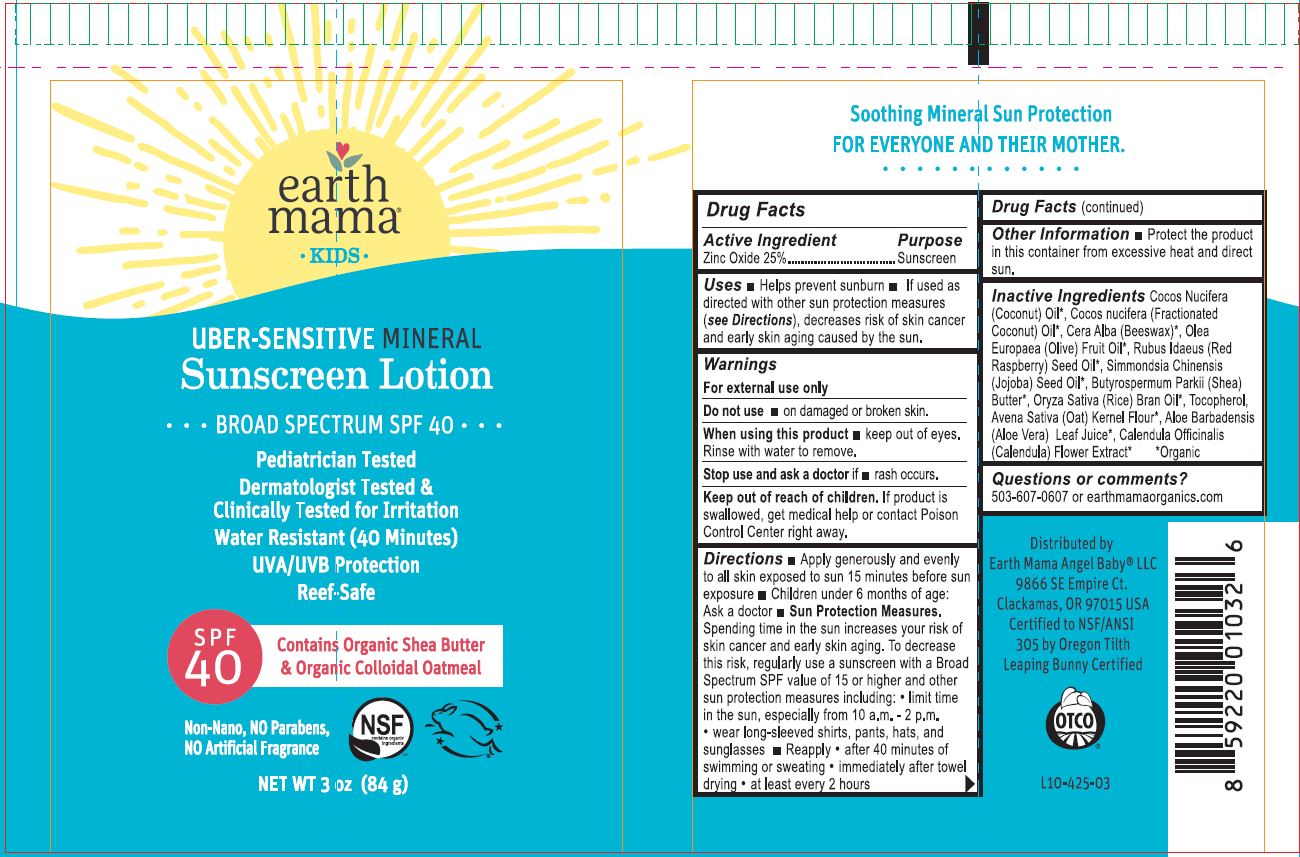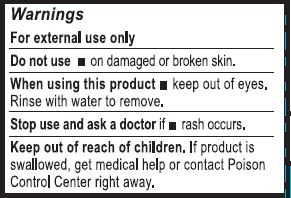 DRUG LABEL: SUNSCREEN
NDC: 62932-172 | Form: OINTMENT
Manufacturer: Private Label Select Ltd CO
Category: otc | Type: HUMAN OTC DRUG LABEL
Date: 20220104

ACTIVE INGREDIENTS: ZINC OXIDE 25 g/100 g
INACTIVE INGREDIENTS: CAPRYLIC/CAPRIC/LAURIC TRIGLYCERIDE; YELLOW WAX; RASPBERRY SEED OIL; TOCOPHEROL; OLEA EUROPAEA FRUIT VOLATILE OIL; SIMMONDSIA CHINENSIS SEED WAX; SHEA BUTTER; OATMEAL; ALOE VERA LEAF; CALENDULA OFFICINALIS FLOWER; COCONUT OIL; RICE BRAN OIL

Kids UberSensative Sunscreen SPF40 Lotion